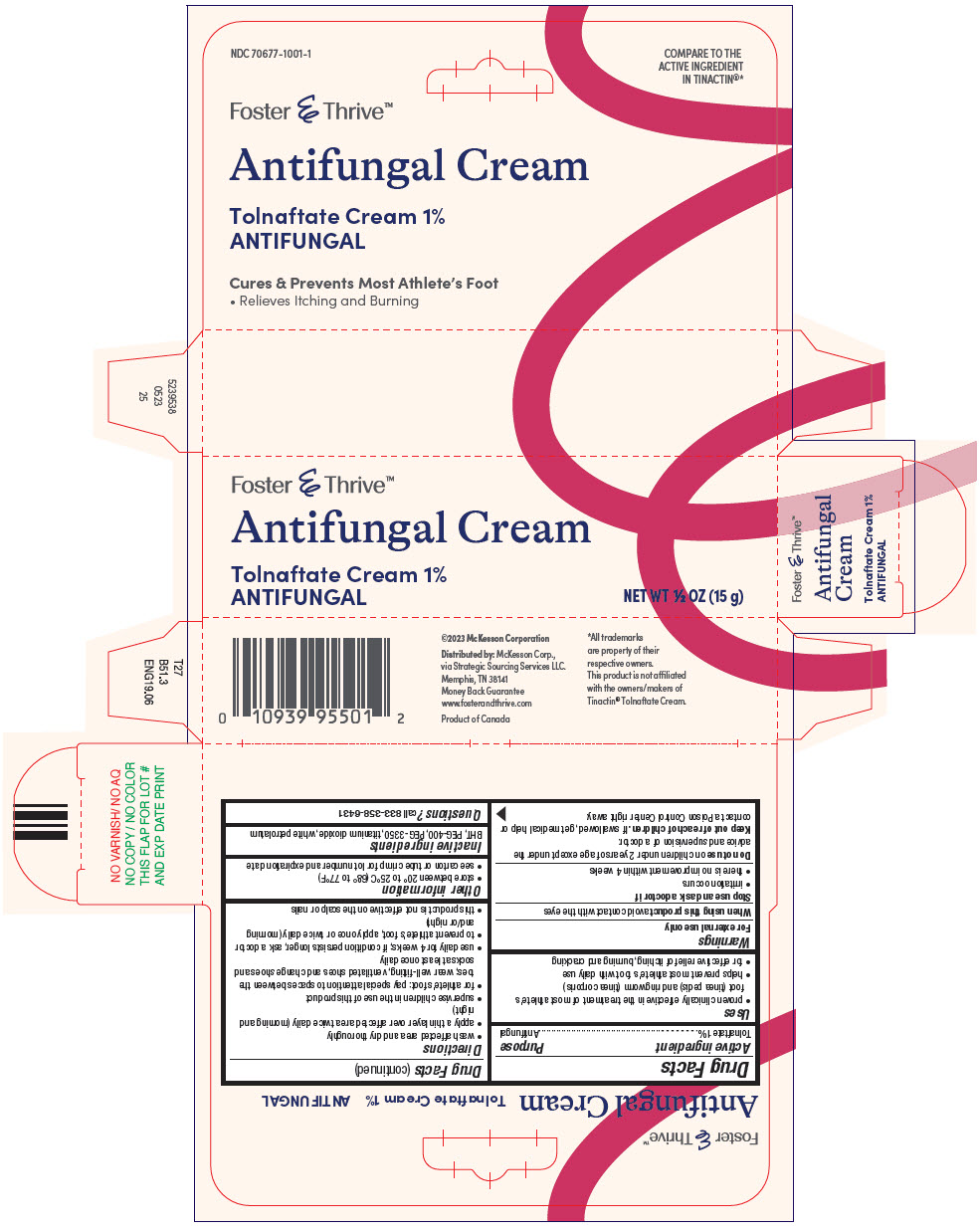 DRUG LABEL: Tolnaftate Antifungal
NDC: 70677-1001 | Form: CREAM
Manufacturer: STRATEGIC SOURCING SERVICES LLC
Category: otc | Type: HUMAN OTC DRUG LABEL
Date: 20250715

ACTIVE INGREDIENTS: TOLNAFTATE 1 g/100 g
INACTIVE INGREDIENTS: BUTYLATED HYDROXYTOLUENE; POLYETHYLENE GLYCOL 400; POLYETHYLENE GLYCOL 3350; TITANIUM DIOXIDE; PETROLATUM

Tolnaftate Antifungal

Drug Facts

Active ingredient

Tolnaftate 1%

Purpose

Antifungal

Uses

- proven clinically effective in the treatment of most athlete's foot (tinea pedis) and ringworm (tinea corporis)
- helps prevent most athlete's foot with daily use
- for effective relief of itching, burning and cracking

Warnings

For external use only

When using this productavoid contact with the eyes

Stop use and ask a doctor if

- irritation occurs
- there is no improvement within 4 weeks

DO NOT USE

Do not useon children under 2 years of age except under the advice and supervision of a doctor.

Keep out of reach of children.If swallowed, get medical help or contact a Poison Control Center right away.

Directions

- wash affected area and dry thoroughly
- apply a thin layer over affected area twice daily (morning and night)
- supervise children in the use of this product
- for athlete's foot: pay special attention to spaces between the toes; wear well-fitting, ventilated shoes and change shoes and socks at least once daily
- use daily for 4 weeks; if condition persists longer, ask a doctor
- to prevent athlete's foot, apply once or twice daily (morning and/or night)
- this product is not effective on the scalp or nails

Other information

- store between 20° to 25°C (68° to 77°F)
- see carton or tube crimp for lot number and expiration date

Inactive ingredients

BHT, PEG-400, PEG-3350, titanium dioxide, white petrolatum

Questions?

call 833-358-6431

Distributed by:McKesson Corp.,
via Strategic Sourcing Services LLC.
Memphis, TN 38141

PRINCIPAL DISPLAY PANEL - 15 g Tube Carton

Foster & Thrive™

Antifungal Cream

Tolnaftate Cream 1%
ANTIFUNGAL

NET WT ½ OZ (15 g)